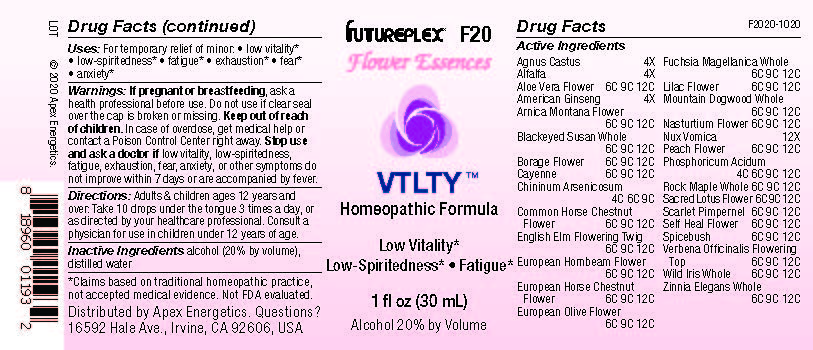 DRUG LABEL: F20
NDC: 63479-0620 | Form: SOLUTION/ DROPS
Manufacturer: Apex Energetics Inc.
Category: homeopathic | Type: HUMAN OTC DRUG LABEL
Date: 20240108

ACTIVE INGREDIENTS: PRUNUS PERSICA FLOWER 12 [hp_C]/1 mL; NELUMBO NUCIFERA FLOWER 12 [hp_C]/1 mL; ANAGALLIS ARVENSIS EXTRACT 12 [hp_C]/1 mL; TROPAEOLUM MAJUS FLOWER 12 [hp_C]/1 mL; PHOSPHORIC ACID 12 [hp_C]/1 mL; ACER NIGRUM WHOLE 12 [hp_C]/1 mL; VERBENA OFFICINALIS FLOWERING TOP 12 [hp_C]/1 mL; AMERICAN GINSENG 4 [hp_X]/1 mL; AESCULUS HIPPOCASTANUM FLOWER 12 [hp_C]/1 mL; BORAGO OFFICINALIS FLOWER 12 [hp_C]/1 mL; CAPSICUM 12 [hp_C]/1 mL; CARPINUS BETULUS FLOWER 12 [hp_C]/1 mL; PRUNELLA VULGARIS FLOWER 12 [hp_C]/1 mL; UMBELLULARIA CALIFORNICA WHOLE 12 [hp_C]/1 mL; IRIS MISSOURIENSIS WHOLE 12 [hp_C]/1 mL; ULMUS PROCERA FLOWERING TWIG 12 [hp_C]/1 mL; OLEA EUROPAEA FLOWER 12 [hp_C]/1 mL; FUCHSIA MAGELLANICA WHOLE 12 [hp_C]/1 mL; QUININE ARSENITE 9 [hp_C]/1 mL; CORNUS NUTTALLII WHOLE 12 [hp_C]/1 mL; RUDBECKIA HIRTA WHOLE 12 [hp_C]/1 mL; SYRINGA VULGARIS FLOWER 12 [hp_C]/1 mL; STRYCHNOS NUX-VOMICA SEED 12 [hp_X]/1 mL; ALOE VERA FLOWER 12 [hp_C]/1 mL; ARNICA MONTANA FLOWER 12 [hp_C]/1 mL; CHASTE TREE 4 [hp_X]/1 mL; ALFALFA 4 [hp_X]/1 mL; ZINNIA ELEGANS WHOLE 12 [hp_C]/1 mL
INACTIVE INGREDIENTS: ALCOHOL; WATER

F20

Active Ingredients
Agnus Castus | 4X
Alfalfa | 4X
Aloe Vera Flower | 6C 9C 12C
American Ginseng | 4X
Arnica Montana Flower | 6C 9C 12C
Blackeyed Susan Whole | 6C 9C 12C
Borage Flower | 6C 9C 12C
Cayenne | 6C 9C 12C
Chininum Arsenicosum | 4C 6C 9C
Common Horse Chestnut Flower | 6C 9C 12C
English Elm Flowering Twig | 6C 9C 12C
European Hornbeam Flower | 6C 9C 12C
European Horse Chestnut Flower | 6C 9C 12C
European Olive Flower | 6C 9C 12C
Fuchsia Magellanica Whole | 6C 9C 12C
Lilac Flower | 6C 9C 12C
Mountain Dogwood Whole | 6C 9C 12C
Nasturtium Flower | 6C 9C 12C
Nux Vomica | 12X
Peach Flower | 6C 9C 12C
Phosphoricum Acidum | 4C 6C 9C 12C
Rock Maple Whole | 6C 9C 12C
Sacred Lotus Flower | 6C 9C 12C
Scarlet Pimpernel | 6C 9C 12C
Self Heal Flower | 6C 9C 12C
Spicebush | 6C 9C 12C
Verbena Officinalis Flowering Top | 6C 9C 12C
Wild Iris Whole | 6C 9C 12C
Zinnia Elegans Whole | 6C 9C 12C

INDICATIONS AND USAGE

Uses:

For temporary relief of minor:

low vitality*

low-spiritedness*

fatigue*

exhaustion*

fear*

anxiety*

*Claims based on traditional homeopathic practice, not accepted medical evidence. Not FDA evaluated.

Warnings:

PREGNANCY OR BREAST FEEDING

If pregnant or breastfeeding, ask a health professional before use.

Do not use if clear seal over the cap is broken or missing.

Keep out of reach of children. In case of overdose, get medical help or contact a Poison Control Center right away.

Stop use and ask a doctor if low vitality, low-spiritedness, fatigue, exhaustion, fear, anxiety, or other symptoms do not improve within 7 days or are accompanied by fever.

Directions:

Adults & children ages 12 years and over: Take 10 drops under the tongue 3 times a day, or as directed by your healthcare professional. Consult a physician for use in children under 12 years of age.

Inactive Ingredients

alcohol (20% by volume), distilled water

Distributed by Apex Energetics. Questions?

16592 Hale Ave., Irvine, CA 92606, USA

PACKAGE LABEL

FUTUREPLEX® F20

Flower Essences

VTLTY™

Low Vitality*

Low-Spiritedness* Fatigue*

1 fl oz (30 mL)

Alcohol 20% by Volume